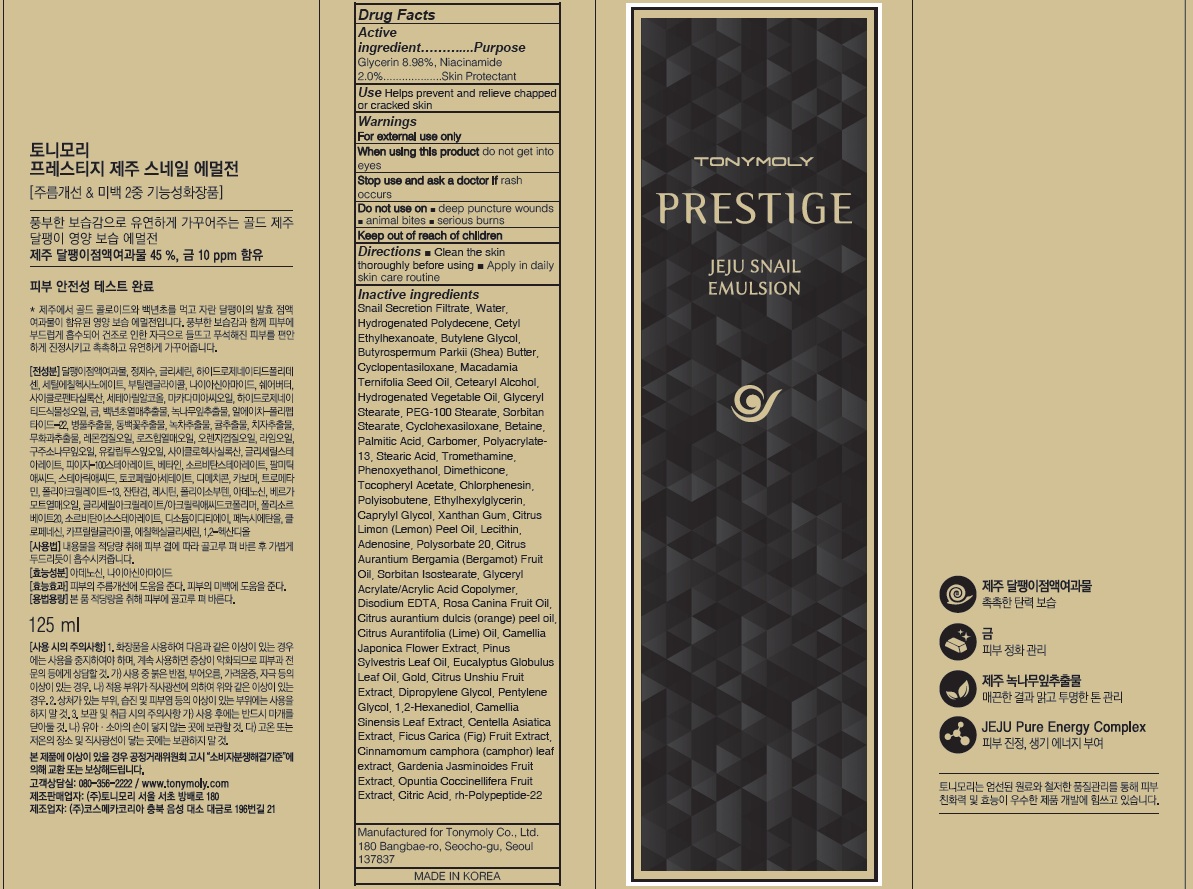 DRUG LABEL: PRESTIGE JEJU SNAIL
NDC: 59078-318 | Form: EMULSION
Manufacturer: TONYMOLY CO.,LTD
Category: otc | Type: HUMAN OTC DRUG LABEL
Date: 20160729

ACTIVE INGREDIENTS: Glycerin 11.22 g/125 mL; Niacinamide 2.50 g/125 mL
INACTIVE INGREDIENTS: Water; Butylene Glycol

ACTIVE INGREDIENT

Active Ingredient: Glycerin 8.98%, Niacinamide 2.0%

INACTIVE INGREDIENT

Inactive Ingredients: Snail Secretion Filtrate, Water, Hydrogenated Polydecene, Cetyl Ethylhexanoate, Butylene Glycol, Butyrospermum Parkii (Shea) Butter, Cyclopentasiloxane, Macadamia Ternifolia Seed Oil, Cetearyl Alcohol, Hydrogenated Vegetable Oil, Glyceryl Stearate, PEG-100 Stearate, Sorbitan Stearate, Cyclohexasiloxane, Betaine, Palmitic Acid, Carbomer, Polyacrylate-13, Stearic Acid, Tromethamine, Phenoxyethanol, Dimethicone, Tocopheryl Acetate, Chlorphenesin, Polyisobutene, Ethylhexylglycerin, Caprylyl Glycol, Xanthan Gum, Citrus Limon (Lemon) Peel Oil, Lecithin, Adenosine, Polysorbate 20, Citrus Aurantium Bergamia (Bergamot) Fruit Oil, Sorbitan Isostearate, Glyceryl Acrylate/Acrylic Acid Copolymer, Disodium EDTA, Rosa Canina Fruit Oil, Citrus aurantium dulcis (orange) peel oil, Citrus Aurantifolia (Lime) Oil, Camellia Japonica Flower Extract, Pinus Sylvestris Leaf Oil, Eucalyptus Globulus Leaf Oil, Gold, Citrus Unshiu Fruit Extract, Dipropylene Glycol, Pentylene Glycol, 1,2-Hexanediol, Camellia Sinensis Leaf Extract, Centella Asiatica Extract, Ficus Carica (Fig) Fruit Extract, Cinnamomum camphora (camphor) leaf extract, Gardenia Jasminoides Fruit Extract, Opuntia Coccinellifera Fruit Extract, Citric Acid, rh-Polypeptide-22

PURPOSE

Purpose: Skin Protectant

WARNINGS

Warnings: For external use only When using this product do not get into eyes, Stop use and ask a doctor if rash occurs Do not use on - deep puncture wounds - animal bites - serious burns Keep out of reach of children

KEEP OUT OF REACH OF CHILDREN

Use

Use: Helps prevent and relieve chapped or cracked skin

Directions

Directions: - Clean the skin thoroughly before using - Apply in daily skin care routine